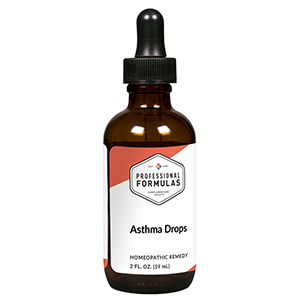 DRUG LABEL: Asthma Drops
NDC: 63083-2010 | Form: LIQUID
Manufacturer: Professional Complementary Health Formulas
Category: homeopathic | Type: HUMAN OTC DRUG LABEL
Date: 20190815

ACTIVE INGREDIENTS: ARALIA RACEMOSA ROOT 3 [hp_X]/59 mL; LOBELIA CARDINALIS WHOLE 3 [hp_X]/59 mL; SPONGIA OFFICINALIS SKELETON, ROASTED 3 [hp_X]/59 mL; ANTIMONY POTASSIUM TARTRATE 8 [hp_X]/59 mL; ACONITUM NAPELLUS WHOLE 6 [hp_X]/59 mL; SUS SCROFA ADRENAL GLAND 6 [hp_X]/59 mL; BLATTA ORIENTALIS 6 [hp_X]/59 mL; COPPER 6 [hp_X]/59 mL; IODINE 6 [hp_X]/59 mL; IPECAC 6 [hp_X]/59 mL; LOBELIA INFLATA WHOLE 6 [hp_X]/59 mL; BEEF LUNG 6 [hp_X]/59 mL; ARSENIC TRIOXIDE 12 [hp_X]/59 mL; SULFUR 12 [hp_X]/59 mL; OYSTER SHELL CALCIUM CARBONATE, CRUDE 30 [hp_X]/59 mL
INACTIVE INGREDIENTS: ALCOHOL; WATER

C10

ACTIVE INGREDIENTS

Aralia racemosa 3X
Lobelia cardinalis 3X
Spongia tosta 3X, 6X
Antimonium tartaricum 8X
Aconitum napellus 6X
Adrenal 6X
Blatta orientalis 6X
Cuprum metallicum 6X
Iodium 6X
Ipecacuanha 6X
Lobelia inflata 6X
Lung 6X
Arsenicum album 12X
Sulphur 12X
Calcarea carbonica 30X

QUESTIONS

Professional Formulas

PO Box 2034 Lake Oswego, OR 97035

INDICATIONS

For the temporary relief of wheezing, coughing, chest tightness or shortness of breath due to aerobic exercise, obesity, anxiousness, smoking, or exposure to pollutants, allergens, or environmental toxins.*

PURPOSE

*Claims based on traditional homeopathic practice, not accepted medical evidence. Not FDA evaluated.

WARNINGS

A persistent cough or chest pain may be signs of a serious condition. Consult a doctor promptly if symptoms persist. Keep out of the reach of children. In case of overdose, get medical help or contact a poison control center right away. If pregnant or breastfeeding, ask a healthcare professional before use.

Keep out of the reach of children.

PREGNANCY OR BREAST FEEDING

If pregnant or breastfeeding, ask a healthcare professional before use.

DIRECTIONS

Place drops under tongue 30 minutes before/after meals. Adults and children 12 years and over: Take 10 drops up to 3 times per day for up to 6 weeks. For immediate onset of symptoms, take 10 to 15 drops every 15 minutes up to 3 hours. For less severe symptoms, take 10-15 drops hourly up to 8 hours. Consult a physician for use in children under 12 years of age.

OTHER INFORMATION

Tamper resistant. If seal is broken, do not use. After opening, close container tightly and store at room temperature away from heat.

INACTIVE INGREDIENTS

20% ethanol, purified water.

LABEL

Est 1985

Professional Formulas

Complementary Health

Asthma Drops

Homeopathic Remedy

2 FL. OZ. (59 mL)